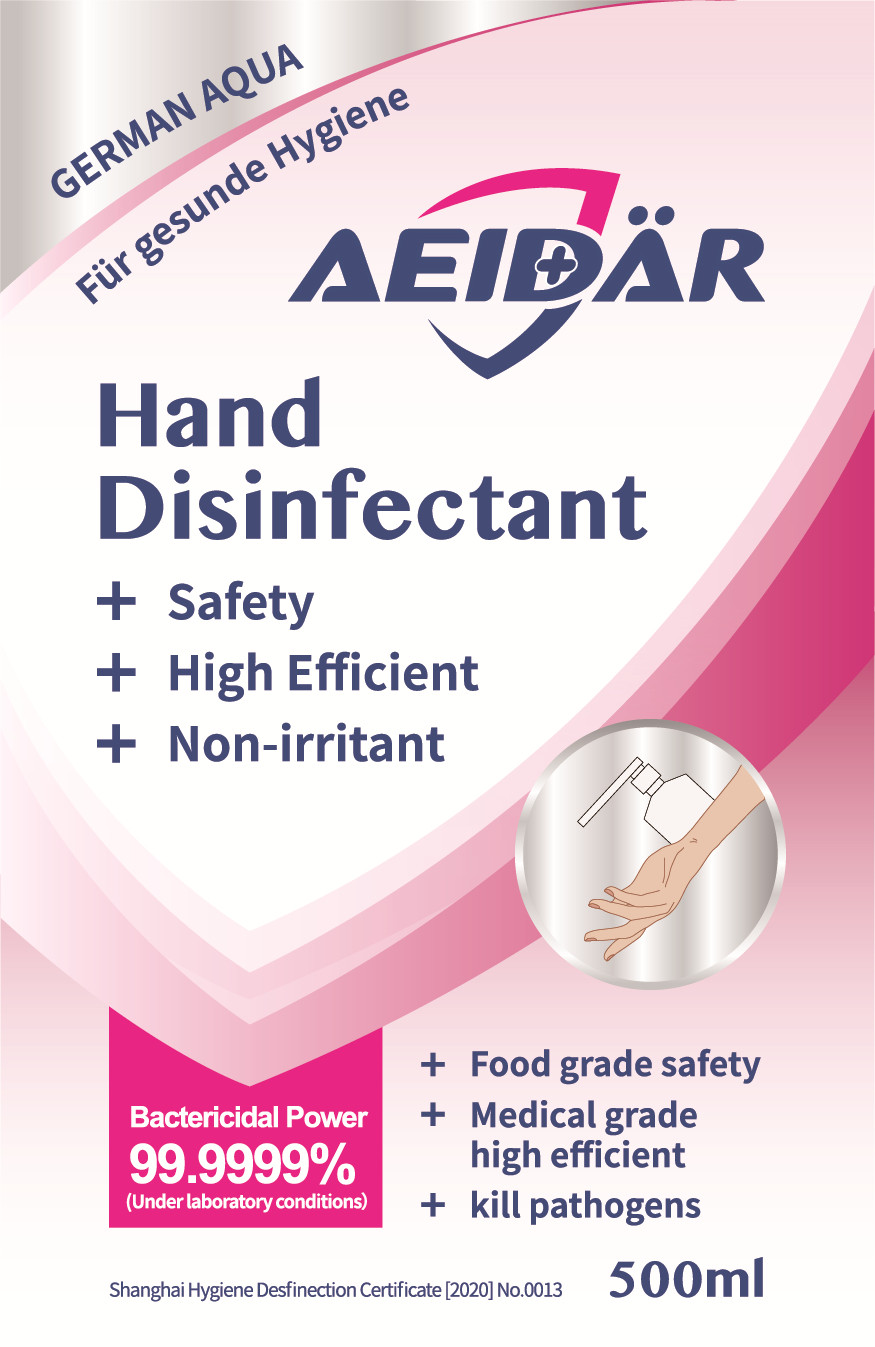 DRUG LABEL: Aeidar Hand Disinfectant
NDC: 66268-001 | Form: LIQUID
Manufacturer: Shanghai Yishu Biotechnology Co., Ltd.
Category: otc | Type: HUMAN OTC DRUG LABEL
Date: 20200609

ACTIVE INGREDIENTS: HYPOCHLOROUS ACID 0.15 g/500 mL
INACTIVE INGREDIENTS: WATER

DOSAGE AND ADMINISTRATION

Room temperature preservation and keep off the sun.

INACTIVE INGREDIENT

Purified water

INDICATIONS AND USAGE

Direct spray on hands and where need to be sterilized. It can be dried without flushing.

ACTIVE INGREDIENT

Hypochlorous acid

keep out of reach of children

PURPOSE

Disinfection
Sterilization
No Rinseing

WARNINGS

Do not replace container. Do not mix with other disinfection products.